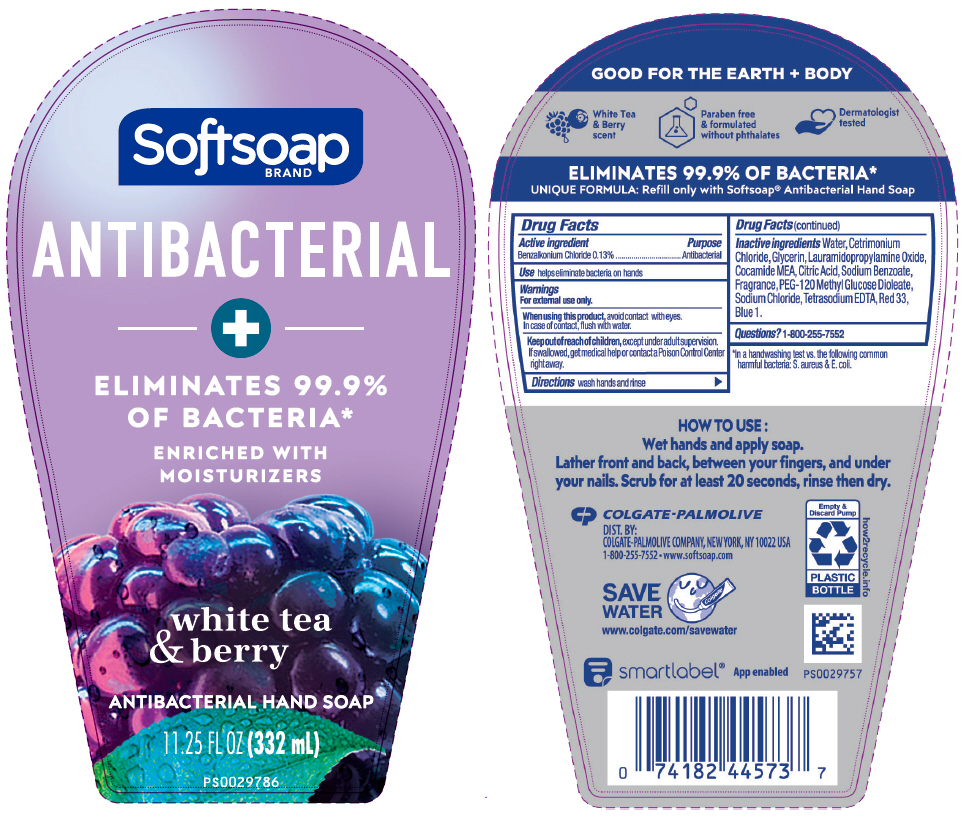 DRUG LABEL: SOFTSOAP ANTIBACTERIAL WITH MOISTURIZERS WHITE TEA AND BERRY LHS
NDC: 35000-249 | Form: LIQUID
Manufacturer: Colgate-Palmolive Company
Category: otc | Type: HUMAN OTC DRUG LABEL
Date: 20241213

ACTIVE INGREDIENTS: BENZALKONIUM CHLORIDE 1.33 mg/1 mL
INACTIVE INGREDIENTS: WATER; CETRIMONIUM CHLORIDE; GLYCERIN; LAURAMIDOPROPYLAMINE OXIDE; COCO MONOETHANOLAMIDE; ANHYDROUS CITRIC ACID; SODIUM BENZOATE; PEG-120 METHYL GLUCOSE DIOLEATE; SODIUM CHLORIDE; EDETATE SODIUM

Softsoap Antibacterial with Moisturizers White Tea & Berry LHS

Drug Facts

Active ingredient

Benzalkonium Chloride 0.13%

Purpose

Antibacterial

Use

helps eliminate bacteria on hands

Warnings

For external use only.

When using this product, avoid contact with eyes.

In case of contact, flush with water.

Keep out of reach of children, except under adult supervision. If swallowed, get medical help or contact a Poison Control Center right away.

Directions

wash hands and rinse

Inactive ingredients

Water, Cetrimonium Chloride, Glycerin, Lauramidopropylamine Oxide, Cocamide MEA, Citric Acid, Sodium Benzoate, Fragrance, PEG-120 Methyl Glucose Dioleate, Sodium Chloride, Tetrasodium EDTA, Red 33, Blue 1.

Questions?

1-800-255-7552

DIST. BY:
COLGATE-PALMOLIVE COMPANY, NEW YORK, NY 10022 USA

PRINCIPAL DISPLAY PANEL - 332 mL Bottle Label

Softsoap
BRAND

ANTIBACTERIAL
+
ELIMINATES 99.9%
OF BACTERIA*

ENRICHED WITH
MOISTURIZERS

white tea
& berry

ANTIBACTERIAL HAND SOAP

11.25 FL OZ (332 mL)

PS0029786